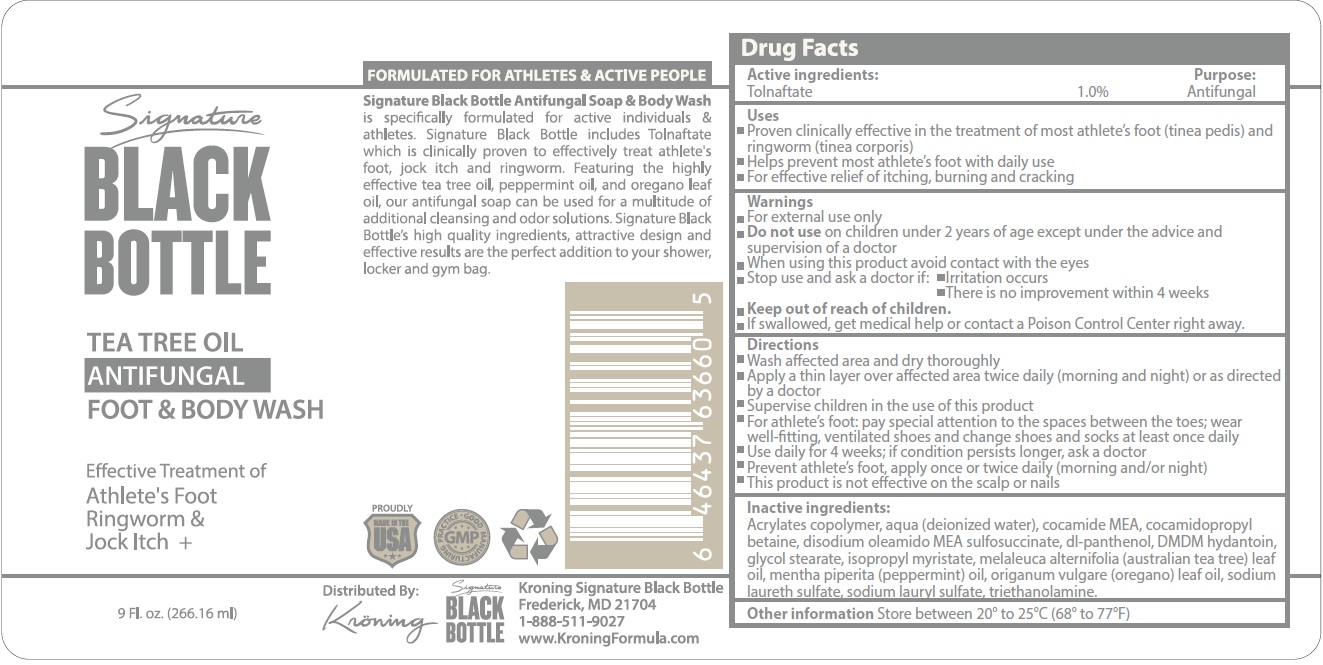 DRUG LABEL: Signature Black Bottle Tea Tree Antifungal Foot and Body Wash
NDC: 69882-726 | Form: LOTION
Manufacturer: Restoration Rockstar, Llc (dba: Kroning Signature Black Bottle)
Category: otc | Type: HUMAN OTC DRUG LABEL
Date: 20231110

ACTIVE INGREDIENTS: TOLNAFTATE 10 mg/1 mL
INACTIVE INGREDIENTS: WATER; COCO MONOETHANOLAMIDE; COCAMIDOPROPYL BETAINE; DISODIUM OLEAMIDO MONOETHANOLAMINE SULFOSUCCINATE; PANTHENOL; DMDM HYDANTOIN; GLYCOL STEARATE; ISOPROPYL MYRISTATE; TEA TREE OIL; PEPPERMINT OIL; OREGANO LEAF OIL; SODIUM LAURETH SULFATE; SODIUM LAURYL SULFATE; TROLAMINE

Signature Black Bottle Tea Tree Antifungal Foot & Body Wash

Active ingredients:

Tolnaftate 1.0%

Purpose:

Antifungal

Uses

- Proven clinically effective in the treatment of most athlete's foot (tinea pedis) and ringworm (tinea corporis)
- Helps prevent most athlete's foot with daily use
- For effective relief of itching, burning and cracking

Warnings

For external use only

Do not use

on children under 2 years of age except under the advice and supervision of a doctor

When using this product

avoid contact with the eyes

Stop use and ask a doctor if:

- Irritation occurs
- There is no improvement within 4 weeks

Keep out of reach of children.

If swallowed, get medical help or contact a Poison Control Center right away.

Directions

- Wash affected area and dry thoroughly
- Apply a thin layer over affected area twice daily (morning and night) or as directed by a doctor
- Supervise children in the use of this product
- For athlete's foot: pay special attention to the spaces between the toes; wear well-fitting, ventilated shoes and change shoes and socks at least once daily
- Use daily for 4 weeks; if condition persists longer, ask a doctor
- Prevent athlete's foot, apply once or twice daily (morning and/or night
- This product is not effective on the scalp or nails

Inactive ingredients:

Acrylates copolymer, aqua (deionized water), cocamide MEA, cocamidopropyl betaine, disodium oleamido MEA sulfosuccinate, dl-panthenol, DMDM hydantoin, glycol stearate, isopropyl myristate, melaleuca alternifolia (australian tea tree) leaf oil, mentha piperita (peppermint) oil, origanum vulgare (oregano) leaf oil, sodium laureth sulfate, sodium lauryl sulfate, triethanolamine.

Other information

Store between 20° to 25°C (68° to 77°F)